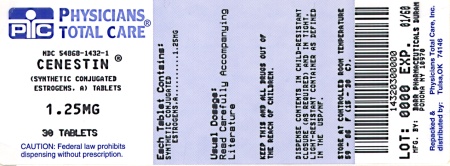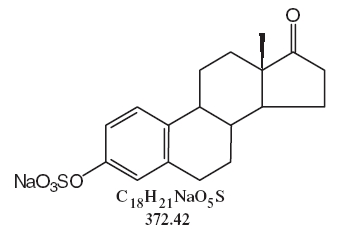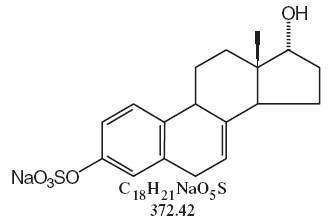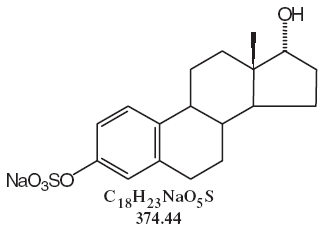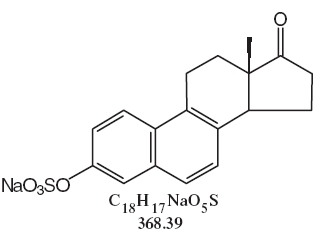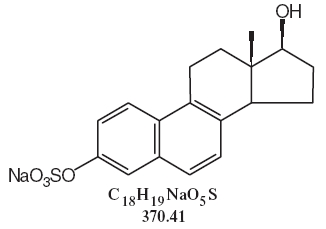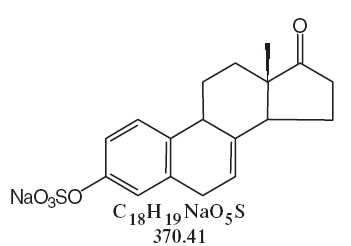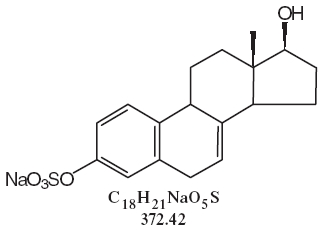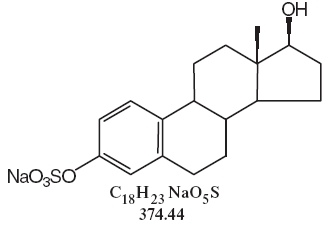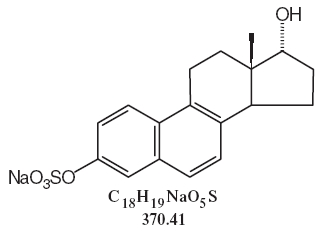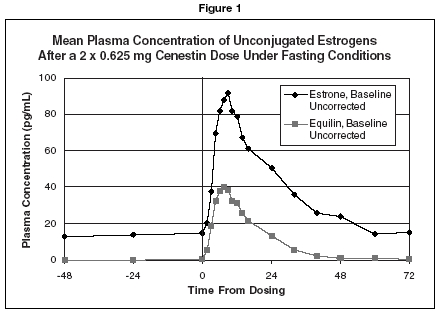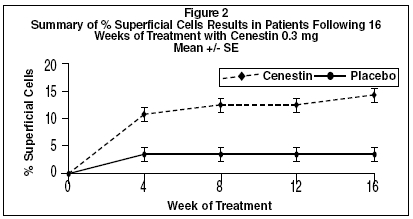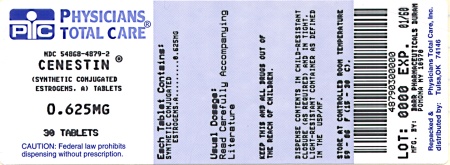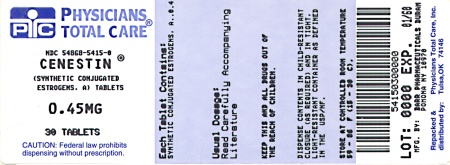 DRUG LABEL: Cenestin
NDC: 54868-5415 | Form: TABLET, FILM COATED
Manufacturer: Physicians Total Care, Inc.
Category: prescription | Type: HUMAN PRESCRIPTION DRUG LABEL
Date: 20040901

ACTIVE INGREDIENTS: ESTROGENS, CONJUGATED SYNTHETIC A 0.45 mg/1 1
INACTIVE INGREDIENTS: ETHYLCELLULOSES; HYPROMELLOSES; LACTOSE MONOHYDRATE; MAGNESIUM STEARATE; POLYETHYLENE GLYCOL; POLYSORBATE 80; STARCH, CORN; TITANIUM DIOXIDE; TRIETHYL CITRATE; FD&C YELLOW NO. 6

Cenestin®
(synthetic conjugated estrogens, A) Tablets

Rx only

Revised SEPTEMBER 2004

11000422506

ESTROGENS INCREASE THE RISK OF ENDOMETRIAL CANCER

Close clinical surveillance of all women taking estrogens is important. Adequate diagnostic measures, including endometrial sampling when indicated, should be undertaken to rule out malignancy in all cases of undiagnosed persistent or recurring abnormal vaginal bleeding. There is no evidence that the use of “natural” estrogens results in a different endometrial risk profile than synthetic estrogens at equivalent estrogen doses. (See WARNINGS, Malignant neoplasms, Endometrial cancer.)

CARDIOVASCULAR AND OTHER RISKS

Estrogens with and without progestins should not be used for the prevention of cardiovascular disease. (See WARNINGS, Cardiovascular disorders.)

The Women’s Health Initiative (WHI) study reported increased risks of myocardial infarction, stroke, invasive breast cancer, pulmonary emboli, and deep vein thrombosis in postmenopausal women (50 to 79 years of age) during 5 years of treatment with oral conjugated equine estrogens (CE 0.625 mg) combined with medroxyprogesterone acetate (MPA 2.5 mg) relative to placebo. (See CLINICAL PHARMACOLOGY, Clinical Studies.)

The Women’s Health Initiative Memory Study (WHIMS), a substudy of WHI, reported increased risk of developing probable dementia in postmenopausal women 65 years of age or older during 4 years of treatment with oral conjugated estrogens plus medroxyprogesterone acetate relative to placebo. It is unknown whether this finding applies to younger postmenopausal women. (See CLINICAL PHARMACOLOGY, Clinical Studies.)

Other doses of oral conjugated estrogens with medroxyprogesterone acetate, and other combinations and dosage forms of estrogens and progestins were not studied in the WHI clinical trials and, in the absence of comparable data, these risks should be assumed to be similar. Because of these risks, estrogens with or without progestins should be prescribed at the lowest effective doses and for the shortest duration consistent with treatment goals and risks for the individual woman.

DESCRIPTION

Synthetic conjugated estrogens, A tablets contain a blend of nine (9) synthetic estrogenic substances. The estrogenic substances are sodium estrone sulfate, sodium equilin sulfate, sodium 17α-dihydroequilin sulfate, sodium 17α-estradiol sulfate, sodium 17β-dihydroequilin sulfate, sodium 17α-dihydroequilenin sulfate, sodium 17β-dihydroequilenin sulfate, sodium equilenin sulfate and sodium 17β-estradiol sulfate.

The structural formulae for these estrogens are:

Sodium Estrone Sulfate
Sodium 17α-Dihydroequilin Sulfate
Sodium 17α-Estradiol Sulfate
Sodium Equilenin Sulfate
Sodium 17β-Dihydroequilenin Sulfate
Sodium Equilin Sulfate
Sodium 17β-Dihydroequilin Sulfate
Sodium 17β-Estradiol Sulfate
Sodium 17α-Dihydroequilenin Sulfate

Tablets for oral administration, are available in 0.3 mg, 0.45 mg, 0.625 mg, 0.9 mg and 1.25 mg strengths of synthetic conjugated estrogens, A. Tablets also contain the following inactive ingredients: ethylcellulose, hypromellose, lactose monohydrate, magnesium stearate, polyethylene glycol, polysorbate 80, pregelatinized starch, titanium dioxide, and triethyl citrate.

-0.3 mg tablets also contain FD&C Blue No. 2 aluminum lake and D&C Yellow No. 10 aluminum lake.

-0.45 mg tablets also contain FD&C Yellow No. 6/Sunset Yellow FCF lake.

-0.625 mg tablets also contain FD&C Red No. 40 aluminum lake.

-0.9 mg tablets do not contain additional color additives.

-1.25 mg tablets also contain FD&C Blue No. 2 aluminum lake.

CLINICAL PHARMACOLOGY

Endogenous estrogens are largely responsible for the development and maintenance of the female reproductive system and secondary sexual characteristics. Although circulating estrogens exist in a dynamic equilibrium of metabolic interconversions, estradiol is the principal intracellular human estrogen and is substantially more potent than its metabolites, estrone and estriol at the receptor level.

The primary source of estrogen in normally cycling adult women is the ovarian follicle, which secretes 70 to 500 mcg of estradiol daily, depending on the phase of the menstrual cycle. After menopause, most endogenous estrogen is produced by conversion of androstenedione, secreted by the adrenal cortex, to estrone by peripheral tissues. Thus, estrone and the sulfate-conjugated form, estrone sulfate, are the most abundant circulating estrogens in postmenopausal women.

Estrogens act through binding to nuclear receptors in estrogen-responsive tissues. To date, two estrogen receptors have been identified. These vary in proportion from tissue to tissue.

Circulating estrogens modulate the pituitary secretion of the gonadotropins, luteinizing hormone (LH) and follicle stimulating hormone (FSH) through a negative feedback mechanism. Estrogens act to reduce the elevated levels of these hormones seen in postmenopausal women.

Pharmacokinetics

Absorption

Synthetic conjugated estrogens, A are soluble in water and are well absorbed from the gastrointestinal tract after release from the drug formulation. The Cenestin tablet releases the synthetic conjugated estrogens, A slowly over a period of several hours. The effect of food on the bioavailability of synthetic conjugated estrogens, A from Cenestin has not been studied.

Table 1 PHARMACOKINETIC PARAMETERS FOR UNCONJUGATED AND CONJUGATED ESTROGENS IN HEALTHY POSTMENOPAUSAL WOMEN UNDER FASTING CONDITIONS
Pharmacokinetic Parameters of Unconjugated Estrogens Following a
Dose of 2 x 0.625 mg Cenestin
Drug | Cmax (pg/mL) CV% | Tmax (h) CV% | AUC0-72h (pg•hr/mL) CV%
Baseline-corrected estrone | 84.5 (41.7) | 8.25 (35.6) | 1749 (43.8)
Equilin | 45.6 (47.3) | 7.78 (28.8) | 723 (67.9)

Pharmacokinetic Parameters of Conjugated Estrogens Following a
Dose of 2 x 0.625 mg Cenestin
Drug | Cmax (pg/mL) CV% | Tmax (h) CV% | t ½ (h) CV% | AUC0-72h (pg•hr/mL) CV%
Baseline-corrected estrone | 4.43 (40.4) | 7.7 (30.3) | 10.6 (25.4) | 69.89 (39.2)
Equilin | 3.27 (43.5) | 5.8 (31.1) | 9.7 (23.0) | 46.46 (47.5)

Distribution

The distribution of exogenous estrogens is similar to that of endogenous estrogens. Estrogens are widely distributed in the body and are generally found in higher concentrations in the sex hormone target organs. Estrogens circulate in the blood largely bound to sex hormone binding globulin (SHBG) and albumin.

Metabolism

Exogenous estrogens are metabolized in the same manner as endogenous estrogens. Circulating estrogens exist in a dynamic equilibrium of metabolic interconversions. These transformations take place mainly in the liver. Estradiol is converted reversibly to estrone, and both can be converted to estriol, which is the major urinary metabolite. Estrogens also undergo enterohepatic recirculation via sulfate and glucuronide conjugation in the liver, biliary secretion of conjugates into the intestine, and hydrolysis in the gut followed by reabsorption. In postmenopausal women a significant portion of the circulating estrogens exist as sulfate conjugates, especially estrone sulfate, which serves as a circulating reservoir for the formation of more active estrogens.

Excretion

Estradiol, estrone, and estriol are excreted in the urine along with glucuronide and sulfate conjugates.

Special Populations

Cenestin was investigated in postmenopausal women. No pharmacokinetic studies were conducted in special populations, including patients with renal or hepatic impairment.

Drug Interactions

In vitro and in vivo studies have shown that estrogens are metabolized partially by cytochrome P450 3A4 (CYP3A4). Therefore, inducers and inhibitors of CYP3A4 may affect estrogen drug metabolism. Inducers of CYP3A4 such as St. John’s Wort preparations (Hypericum perforatum), phenobarbital, carbamazepine, and rifampin may reduce plasma concentrations of estrogens, possibly resulting in a decrease in therapeutic effects and/or changes in the uterine bleeding profile. Inhibitors of CYP3A4 such as erythromycin, clarithromycin, ketoconazole, itraconazole, ritonavir and grapefruit juice may increase plasma concentrations of estrogens and may result in side effects.

Clinical Studies

Effects on vasomotor symptoms

A randomized, placebo-controlled multicenter clinical study was conducted evaluating the effectiveness of Cenestin for the treatment of moderate to severe vasomotor symptoms in 120 postmenopausal women between 38 and 66 years of age (68% were Caucasian). Patients were randomized to receive either placebo or 0.625 mg Cenestin daily for 12 weeks. Dose titration was allowed after one week of treatment. The starting dose was either doubled (2 x 0.625 mg Cenestin or placebo taken daily) or reduced (0.3 mg Cenestin or placebo taken daily), if necessary. Efficacy was assessed at 4 and 12 weeks of treatment. By week 12, 10% of the study participants remained on a single 0.625 mg Cenestin tablet daily while 77% required two (0.625 mg) tablets daily. The results in Table 2 indicate that compared to placebo, Cenestin produced a reduction in moderate to severe vasomotor symptoms at weeks 4 and 12.

A second randomized, placebo-controlled multicenter clinical study was conducted evaluating the effectiveness of 0.45 mg Cenestin tablets, for the treatment of moderate to severe vasomotor symptoms in 104 menopausal women between 52 and 74 years of age (76% were Caucasian). Patients were randomized to receive either placebo or 0.45 mg Cenestin daily for 12 weeks. Efficacy was assessed at 4 and 12 weeks of treatment. The mean change in the number of moderate to severe hot flushes per week shown in Table 3 indicate that compared to placebo, 0.45 mg Cenestin produced a reduction in moderate to severe vasomotor symptoms at weeks 4 and 12. A corresponding reduction in the severity of hot flushes was demonstrated at weeks 5 and 12.

Table 2 Clinical Response Mean Change in the Number of Moderate to Severe Hot Flushes Per Week, 0.625 mg and 2 x 0.625 mg Cenestin, ITT Population
 | Cenestin 0.625 mg and 2 x 0.625 mg (n=70) | Placebo (n=47)
Baseline
Mean # (SD) | 96.8 (42.6) | 94.1 (33.9)
Week 4
Mean # (SD) | 28.7 (28.8) | 45.7 (36.8)
Mean Change from Baseline (SD) | -68.1 (43.9) | -48.4 (46.2)
P-value vs. Placebo | p=.022
Week 12
Mean # (SD) | 16.5 (25.7) | 37.8 (38.7)
Mean Change from Baseline (SD) | -80.3 (50.3) | -56.3 (48.0)
P-value vs. Placebo | p=0.10
Mean = Arithmetic Mean, SD = Standard Deviation

Table 3 Clinical Response Mean Change in the Number of Moderate to Severe Hot Flushes Per Week, 0.45 mg Cenestin, ITT Population
 | Cenestin 0.45 mg (n=53) | Placebo (n=51)
Baseline
Mean # (SD) | 95.9 (37.0) | 95.9 (41.6)
Week 4
Mean # (SD) | 45.7 (45.9) | 59.4 (46.2)
Mean Change from Baseline (SD) | -50.3 (35.4) | -36.5 (42.9)
P-value vs. Placebo | p=0.14
Week 12
Mean # (SD) | 26.1 (43.0) | 50.5 (48.4)
Mean Change from Baseline (SD) | -69.9 (38.1) | -45.4 (44.7)
P-value vs. Placebo | p<.001
Mean = Arithmetic Mean, SD = Standard Deviation

Effects on vulvar and vaginal atrophy

The effects of 0.3 mg Cenestin on moderate to severe symptoms of vulvar and vaginal atrophy were confirmed in a 16-week, randomized, placebo-controlled, multicenter clinical study in 72 postmenopausal women between 30 and 77 years of age (53% were Caucasian). Patients were randomized to receive either placebo or 0.3 mg Cenestin daily for 16 weeks. Efficacy was assessed at weeks 12 and 16 for vaginal wall cytology and week 16 for vaginal pH. Results for percent of superficial cells from a maturation index of the vaginal mucosa are shown in Figure 2. Mean vaginal pH decreased from a baseline of 6.20 to 5.14 for Cenestin and increased to 6.15 from a baseline of 6.03 for placebo.

Women’s Health Initiative Studies.

The Women’s Health Initiative (WHI) enrolled a total of 27,000 predominantly healthy postmenopausal women to assess the risks and benefits of either the use of oral 0.625 mg conjugated equine estrogens (CE) per day alone or the use of oral 0.625 mg conjugated estrogens plus 2.5 mg medroxyprogesterone acetate (MPA) per day compared to placebo in the prevention of certain chronic diseases. The primary endpoint was the incidence of coronary heart disease (CHD) (nonfatal myocardial infarction and CHD death), with invasive breast cancer as the primary adverse outcome studied. A “global index” included the earliest occurrence of CHD, invasive breast cancer, stroke, pulmonary embolism (PE), endometrial cancer, colorectal cancer, hip fracture, or death due to other cause. The study did not evaluate the effects of CE or CE/MPA on menopausal symptoms.

The CE/MPA substudy was stopped early because, according to the predefined stopping rule, the increased risk of breast cancer and cardiovascular events exceeded the specified benefits included in the “global index.” Results of the CE/MPA substudy, which included 16,608 women (average age of 63 years range 50 to 79; 83.9% White, 6.5% Black, 5.5% Hispanic), after an average follow-up of 5.2 years are presented in Table 4 below:

Table 4 Relative and Absolute Risk Seen in the Estrogen/Progestin Substudy of the WHI
Event [a subset of the events was combined in a “global index,” defined as the earliest occurrence of CHD events, invasive breast cancer, stroke, pulmonary embolism, endometrial cancer, colorectal cancer, hip fracture, or death due to other causes.] | Relative Risk Conjugated Equine Estrogens/Medroxyprogesterone Acetate vs Placebo at 5.2 years (95% CI) | Placebo n - 8102 | CE/MPA n = 8506
Event [a subset of the events was combined in a “global index,” defined as the earliest occurrence of CHD events, invasive breast cancer, stroke, pulmonary embolism, endometrial cancer, colorectal cancer, hip fracture, or death due to other causes.] | Relative Risk Conjugated Equine Estrogens/Medroxyprogesterone Acetate vs Placebo at 5.2 years (95% CI) | Absolute Risk per 10,000 Person-years
CHD events; Non-fatal MI CHD death | 1.29 (1.02-1.63) 1.32 (1.02-1.72) 1.18 (0.70-1.97) | 30 23 6 | 37 30 7
Invasive breast cancer | 1.26 (1.00-1.59) | 30 | 38
Stroke | 1.41 (1.07-1.85) | 21 | 29
Pulmonary embolism | 2.13 (1.39-3.25) | 8 | 16
Colorectal cancer | 0.63 (0.43-0.92) | 16 | 10
Endometrial cancer | 0.83 (0.47-1.47) | 6 | 5
Hip fracture | 0.66 (0.45-0.98) | 15 | 10
Death due to causes other than the events above | 0.92 (0.74-1.14) | 40 | 37
Global index | 1.15 (1.03-1.28) | 151 | 170
Deep vein thrombosis [not included in Global Index.] | 2.07 (1.49-2.87) | 13 | 26
Vertebral fractures | 0.66 (0.44-0.98) | 15 | 9
Other osteoporotic fractures | 0.77 (0.69-0.86) | 170 | 131

For those outcomes included in the “global index,” absolute excess risks per 10,000 person-years in the group treated with CE/MPA were 7 more CHD events, 8 more strokes, 8 more PEs, and 8 more invasive breast cancers, while absolute risk reductions per 10,000 women-years were 6 fewer colorectal cancers and 5 fewer hip fractures. The absolute excess risk of events included in the “global index” was 19 per 10,000 women-years. There was no difference between the groups in terms of all-cause mortality. (See BOXED WARNINGS, WARNINGS, and PRECAUTIONS.)

Women's Health Initiative Memory Study

The Women’s Health Initiative Memory Study (WHIMS), a sub-study of WHI, enrolled 4,532 predominantly healthy postmenopausal women 65 years of age and older (47% were age 65 to 69 years, 35% were 70 to 74 years, and 18% were 75 years of age and older) to evaluate the effects of CE/MPA (0.625 mg conjugated estrogens plus 2.5 mg medroxyprogesterone acetate) on the incidence of probable dementia (primary outcome) compared with placebo.

After an average follow-up of 4 years, 40 women in the estrogen/progestin group (45 per 10,000 women-years) and 21 in the placebo group (22 per 10,000 women-years) were diagnosed with probable dementia. The relative risk of probable dementia in the hormone therapy group was 2.05 (95% CI, 1.21 to 3.48) compared to placebo. Differences between groups became apparent in the first year of treatment. It is unknown whether this finding applies to younger postmenopausal women. (See BOXED WARNING and WARNINGS, Dementia.)

INDICATIONS AND USAGE

Cenestin therapy is indicated for the:

1. Treatment of moderate-to-severe vasomotor symptoms associated with the menopause.

- 0.45 mg Cenestin
- 0.625 mg Cenestin
- 0.9 mg Cenestin
- 1.25 mg Cenestin

2. Treatment of moderate to severe symptoms of vulvar and vaginal atrophy associated with the menopause. When prescribing solely for the treatment of symptoms of vulvar and vaginal atrophy, topical vaginal products should be considered.

- 0.3 mg Cenestin

CONTRAINDICATIONS

Cenestin should not be used in women with any of the following conditions:

1. Undiagnosed abnormal genital bleeding.
2. Known, suspected, or history of cancer of the breast.
3. Known or suspected estrogen-dependent neoplasia.
4. Active deep vein thrombosis, pulmonary embolism or a history of these conditions.
5. Active or recent (e.g., within the past year) arterial thromboembolic disease (e.g., stroke, myocardial infarction).
6. Liver dysfunction or disease.
7. Cenestin therapy should not be used in patients with known hypersensitivity to its ingredients.
8. Known or suspected pregnancy. There is no indication for Cenestin in pregnancy. There appears to be little or no increased risk of birth defects in children born to women who have used estrogens and progestins from oral contraceptives inadvertently during early pregnancy. (See PRECAUTIONS.)

WARNINGS

See BOXED WARNINGS.

1. Cardiovascular disorders.

Estrogen and estrogen/progestin therapy has been associated with an increased risk of cardiovascular events such as myocardial infarction and stroke, as well as venous thrombosis and pulmonary embolism (venous thromboembolism or VTE). Should any of these occur or be suspected, estrogens should be discontinued immediately.

Risk factors for arterial vascular disease (e.g., hypertension, diabetes mellitus, tobacco use, hypercholesterolemia, and obesity) and/or venous thromboembolism (e.g., personal history or family history of VTE, obesity, and systemic lupus erythematosus) should be managed appropriately.

a. Coronary heart disease and stroke.

In the Women’s Health Initiative (WHI) study, an increase in the number of strokes has been observed in women receiving CE compared to placebo.

In the CE/MPA substudy of WHI, an increased risk of coronary heart disease (CHD) events (defined as non-fatal myocardial infarction and CHD death) was observed in women receiving CE/MPA compared to women receiving placebo (37 vs. 30 per 10,000 women-years). The increase in risk was observed in year one and persisted. (See CLINICAL PHARMACOLOGY, Clinical Studies.)

In the same substudy of WHI, an increased risk of stroke was observed in women receiving CE/MPA compared to women receiving placebo (29 vs. 21 per 10,000 women-years). The increase in risk was observed after the first year and persisted.

In postmenopausal women with documented heart disease (n = 2,763, average age 66.7 years) a controlled clinical trial of secondary prevention of cardiovascular disease (Heart and Estrogen/Progestin Replacement Study; HERS) treatment with CE/MPA (0.625mg/2.5mg per day) demonstrated no cardiovascular benefit. During an average follow-up of 4.1 years, treatment with CE/MPA did not reduce the overall rate of CHD events in postmenopausal women with established coronary heart disease. There were more CHD events in the CE/MPA-treated group than in the placebo group in year 1, but not during the subsequent years. Two thousand three hundred and twenty one women from the original HERS trial agreed to participate in an open label extension of HERS, HERS II. Average follow-up in HERS II was an additional 2.7 years, for a total of 6.8 years overall. Rates of CHD events were comparable among women in the CE/MPA group and the placebo group in HERS, HERS II, and overall.
Large doses of estrogen (5 mg conjugated estrogens per day), comparable to those used to treat cancer of the prostate and breast, have been shown in a large prospective clinical trial in men to increase the risks of nonfatal myocardial infarction, pulmonary embolism, and thrombophlebitis.

b. Venous thromboembolism (VTE)

In the Women's Health Initiative (WHI) study, an increase in VTE has been observed in women receiving CE compared to placebo.

In the CE/MPA substudy of WHI, a 2-fold greater rate of VTE, including deep venous thrombosis and pulmonary embolism, was observed in women receiving CE/MPA compared to women receiving placebo. The rate of VTE was 34 per 10,000 women-years in the CE/MPA group compared to 16 per 10,000 women-years in the placebo group. The increase in VTE risk was observed during the first year and persisted. (See CLINICAL PHARMACOLOGY, Clinical Studies.)

If feasible, estrogens should be discontinued at least 4 to 6 weeks before surgery of the type associated with an increased risk of thromboembolism, or during periods of prolonged immobilization.

2. Malignant neoplasms.

a. Endometrial cancer.

The use of unopposed estrogens in women with intact uteri has been associated with an increased risk of endometrial cancer. The reported endometrial cancer risk among unopposed estrogen users is about 2- to 12-fold greater than in non-users, and appears dependent on duration of treatment and on estrogen dose. Most studies show no significant increased risk associated with use of estrogens for less than one year. The greatest risk appears associated with prolonged use, with increased risks of 15- to 24-fold for five to ten years or more and this risk has been shown to persist for at least 8 to 15 years after estrogen therapy is discontinued.

Clinical surveillance of all women taking estrogen/progestin combinations is important. Adequate diagnostic measures, including endometrial sampling when indicated, should be undertaken to rule out malignancy in all cases of undiagnosed persistent or recurring abnormal vaginal bleeding. There is no evidence that the use of natural estrogens results in a different endometrial risk profile than synthetic estrogens of equivalent estrogen dose. Adding a progestin to estrogen therapy has been shown to reduce the risk of endometrial hyperplasia, which may be a precursor to endometrial cancer.

b. Breast cancer.

The use of estrogens and progestins by postmenopausal women has been reported to increase the risk of breast cancer. The most important randomized clinical trial providing information about this issue is the Women’s Health Initiative (WHI) substudy of CE/MPA (see CLINICAL PHARMACOLOGY, Clinical Studies). The results from observational studies are generally consistent with those of the WHI clinical trial and report no significant variation in the risk of breast cancer among different estrogens or progestins, doses, or routes of administration.

The CE/MPA sub-study of WHI reported an increased risk of breast cancer in women who took CE/MPA for a mean follow-up of 5.6 years. Observational studies have also reported an increased risk for estrogen/progestin combination therapy, and a smaller increased risk for estrogen alone therapy, after several years of use. In the WHI trial and from observational studies, the excess risk increased with duration of use. From observational studies, the risk appeared to return to baseline in about five years after stopping treatment. In addition, observational studies suggest that the risk of breast cancer was greater, and became apparent earlier, with estrogen/progestin combination therapy as compared to estrogen alone therapy.

In the CE/MPA sub-study, 26% of the women reported prior use of estrogen alone and/or estrogen/progestin combination hormone therapy. After a mean follow-up of 5.6 years during the clinical trial, the overall relative risk of invasive breast cancer was 1.24 (95% confidence interval 1.01-1.54), and the overall absolute risk was 41 vs. 33 cases per 10,000 women-years, for CE/MPA compared with placebo. Among women who reported prior use of hormone therapy, the relative risk of invasive breast cancer was 1.86, and the absolute risk was 46 vs. 25 cases per 10,000 women-years, for CE/MPA compared with placebo. Among women who reported no prior use of hormone therapy, the relative risk of invasive breast cancer was 1.09, and the absolute risk was 40 vs. 36 cases per 10,000 women-years for CE/MPA compared with placebo. In the same sub-study, invasive breast cancers were larger and diagnosed at a more advanced stage in the CE/MPA group compared with the placebo group. Metastatic disease was rare with no apparent difference between the two groups. Other prognostic factors such as histologic subtype, grade and hormone receptor status did not differ between the groups.

The use of estrogen plus progestin has been reported to result in an increase in abnormal mammograms requiring further evaluation. All women should receive yearly breast examinations by a healthcare provider and perform monthly breast self-examinations. In addition, mammography examinations should be scheduled based on patient age, risk factors, and prior mammogram results.

3. Dementia

In the Women’s Health Initiative Memory Study (WHIMS), 4,532 generally healthy postmenopausal women 65 years of age and older were studied, of whom 35% were 70 to 74 years of age and 18% were 75 or older. After an average follow-up of 4 years, 40 women being treated with CE/MPA (1.8%, n = 2,229) and 21 women in the placebo group (0.9%, n = 2,303) received diagnoses of probable dementia. The relative risk for CE/MPA versus placebo was 2.05 (95% confidence interval 1.21 – 3.48), and was similar for women with and without histories of menopausal hormone use before WHIMS. The absolute risk of probable dementia for CE/MPA versus placebo was 45 versus 22 cases per 10,000 women-years, and the absolute excess risk for CE/MPA was 23 cases per 10,000 women-years. It is unknown whether these findings apply to younger postmenopausal women. (See CLINICAL PHARMACOLOGY, Clinical Studies and PRECAUTIONS, Geriatric Use.)

4. Gallbladder disease

A 2 to 4-fold increase in the risk of gallbladder disease requiring surgery in postmenopausal women receiving estrogens has been reported.

5. Hypercalcemia

Estrogen administration may lead to severe hypercalcemia in patients with breast cancer and bone metastases. If hypercalcemia occurs, use of the drug should be stopped and appropriate measures taken to reduce the serum calcium level.

6. Visual abnormalities

Retinal vascular thrombosis has been reported in patients receiving estrogens. Discontinue medication pending examination if there is sudden partial or complete loss of vision, or a sudden onset of proptosis, diplopia, or migraine. If examination reveals papilledema or renal vascular lesions, estrogens should be permanently discontinued.

PRECAUTIONS

A. General

1. Addition of a progestin when a woman has not had a hysterectomy. Studies of the addition of a progestin for 10 or more days of a cycle of estrogen administration, or daily with estrogen in a continuous regimen, have reported a lowered incidence of endometrial hyperplasia than would be induced by estrogen treatment alone. Endometrial hyperplasia may be a precursor to endometrial cancer.
  There are, however, possible risks that may be associated with the use of progestins with estrogens compared to estrogen-alone regimens. These include a possible increased risk of breast cancer.
2. Elevated blood pressure. In a small number of case reports, substantial increases in blood pressure have been attributed to idiosyncratic reactions to estrogens. In a large, randomized, placebo controlled clinical trial, a generalized effect of estrogens on blood pressure was not seen. Blood pressure should be monitored at regular intervals with estrogen use.
3. Hypertriglyceridemia. In patients with pre-existing hypertriglyceridemia, estrogen therapy may be associated with elevations of plasma triglycerides leading to pancreatitis and other complications.
4. Impaired liver function and past history of cholestatic jaundice. Estrogens may be poorly metabolized in patients with impaired liver function. For patients with a history of cholestatic jaundice associated with past estrogen use or with pregnancy, caution should be exercised and in the case of recurrence, medication should be discontinued.
5. Hypothyroidism. Estrogen administration leads to increased thyroid-binding globulin (TBG) levels. Patients with normal thyroid function can compensate for the increased TBG by making more thyroid hormone, thus maintaining free T4 and T3 serum concentrations in the normal range. Patients dependent on thyroid hormone replacement therapy who are also receiving estrogens may require increased doses of their thyroid replacement therapy. These patients should have their thyroid function monitored in order to maintain their free thyroid hormone levels in an acceptable range.
6. Fluid retention. Because estrogens may cause some degree of fluid retention, patients with conditions that might be influenced by this factor, such as a cardiac or renal dysfunction, warrant careful observation when estrogens are prescribed.
7. Hypocalcemia. Estrogens should be used with caution in individuals with severe hypocalcemia.
8. Ovarian cancer. The CE/MPA substudy of WHI reported that estrogen plus progestin increased the risk of ovarian cancer. After an average follow-up of 5.6 years, the relative risk for ovarian cancer for CE/MPA versus placebo was 1.58 (95% confidence interval 0.77-3.24) but was not statistically significant. The absolute risk for CE/MPA versus placebo was 4.2 versus 2.7 cases per 10,000 women-years. In some epidemiologic studies, the use of estrogen alone, in particular for ten or more years, has been associated with an increased risk of ovarian cancer. Other epidemiologic studies have not found these associations.
9. Exacerbation of endometriosis. Endometriosis may be exacerbated with administration of estrogens. A few cases of malignant transformation of residual endometrial implants have been reported in women treated post-hysterectomy with estrogen alone therapy. For patients known to have residual endometriosis post-hysterectomy, the addition of progestin should be considered.
10. Exacerbation of other conditions. Estrogens may cause an exacerbation of asthma, diabetes mellitus, epilepsy, migraine or porphyria, systemic lupus erythematosus, and hepatic hemangiomas and should be used with caution in women with these conditions.

B. Patient Information

Physicians are advised to discuss the PATIENT INFORMATION leaflet with patients for whom they prescribe Cenestin.

C. Laboratory Tests

Estrogen administration should be initiated at the lowest dose for the approved indication and then guided by clinical response, rather than by serum hormone levels (e.g., estradiol, FSH).

D. Drug/Laboratory Test Interactions

1. Accelerated prothrombin time, partial thromboplastin time, and platelet aggregation time; increased platelet count; increased factors II, VII antigen, VIII antigen, VIII coagulant activity, IX, X, XII, VII-X complex, II-VII-X complex, and beta-thromboglobulin; decreased levels of anti-factor Xa and antithrombin III, decreased antithrombin III activity; increased levels of fibrinogen and fibrinogen activity; increased plasminogen antigen and activity.
2. Increased thyroid-binding globulin (TBG) levels leading to increased circulating total thyroid hormone levels, as measured by protein-bound iodine (PBI), T4 levels (by column or by radioimmunoassay) or T3 levels by radioimmunoassay. T3 resin uptake is decreased, reflecting the elevated TBG. Free T4 and free T3 concentrations are unaltered. Patients on thyroid replacement therapy may require higher doses of thyroid hormone.
3. Other binding proteins may be elevated in serum (i.e., corticosteroid binding globulin (CBG), sex hormone-binding globulin (SHBG)) leading to increased total circulating corticosteroids and sex steroids, respectively. Free hormone concentrations may be decreased. Other plasma proteins may be increased (angiotensinogen/renin substrate, alpha-1-antitrypsin, ceruloplasmin).
4. Increased plasma HDL and HDL2 cholesterol subfraction concentrations, reduced LDL cholesterol concentration, increased triglyceride levels.
5. Impaired glucose tolerance.
6. Reduced response to metyrapone test.

E. Carcinogenesis, Mutagenesis, Impairment of Fertility

Long-term continuous administration of estrogen, with and without progestin, in women, with and without a uterus, has shown an increased risk of endometrial cancer, breast cancer, and ovarian cancer. (See BOXED WARNINGS, WARNINGS and PRECAUTIONS.)

Long-term continuous administration of natural and synthetic estrogens in certain animal species increases the frequency of carcinomas of the breast, uterus, cervix, vagina, testis, and liver.

F. Pregnancy

Cenestin should not be used during pregnancy. (See CONTRAINDICATIONS.)

G. Nursing Mothers

Estrogen administration to nursing mothers has been shown to decrease the quantity and quality of the milk. Detectable amounts of estrogens have been identified in the milk of mothers receiving this drug. Caution should be exercised when Cenestin is administered to a nursing woman.

H. Pediatric Use

Cenestin is not indicated in children.

I. Geriatric Use

There have not been sufficient numbers of geriatric patients involved in studies utilizing Cenestin to determine whether those over 65 years of age differ from younger subjects in their response to Cenestin.
In the Women’s Health Initiative Memory Study, including 4,532 women 65 years of age and older, followed for an average of 4 years, 82% (n = 3,729) were 65 to 74 while 18% (n = 803) were 75 and over. Most women (80%) had no prior hormone therapy use. Women treated with conjugated estrogens plus medroxyprogesterone acetate were reported to have a two-fold increase in the risk of developing probable dementia. Alzheimer’s disease was the most common classification of probable dementia in both the conjugated estrogens plus medroxyprogesterone acetate group and the placebo group. Ninety percent of the cases of probable dementia occurred in the 54% of women that were older than 70. (See WARNINGS, Dementia.)

ADVERSE REACTIONS

See BOXED WARNINGS, WARNINGS and PRECAUTIONS.

Because clinical trials are conducted under widely varying conditions, adverse reaction rates observed in the clinical trials of a drug cannot be directly compared to rates in the clinical trials of another drug and may not reflect the rates observed in practice. The adverse reaction information from clinical trials does, however, provide a basis for identifying the adverse events that appear to be related to drug use and for approximating rates.

In a 12-week clinical trial that included 72 women treated with 0.625 mg and 2 x 0.625 mg Cenestin and 48 women treated with placebo, adverse events that occurred at a rate of ≥ 5% are summarized in Table 5.

Table 5 Number (%) of Patients with Adverse Events With ≥ 5% Occurrence Rate By Body System and Treatment Group
Body System Adverse Event | Cenestin 0.625 mg and 2 x 0.625 mg n (%) | Placebo n (%) | Total n (%)
Number of Patients Who Received Medication | 72 (100) | 48 (100) | 120 (100)
Number of Patients With Adverse Events | 68 (94) | 43 (90) | 111 (93)
Number of Patients Without Any Adverse Events | 4 (6) | 5 (10) | 9 (8)
Body As A Whole
Abdominal Pain | 20 (28) | 11 (23) | 31 (26)
Asthenia | 24 (33) | 20 (42) | 44 (37)
Back Pain | 10 (14) | 6 (13) | 16 (13)
Fever | 1 (1) | 3 (6) | 4 (3)
Headache | 49 (68) | 32 (67) | 81 (68)
Infection | 10 (14) | 5 (10) | 15 (13)
Pain | 8 (11) | 9 (19) | 17 (14)
Cardiovascular System
Palpitation | 15 (21) | 13 (27) | 28 (23)
Digestive System
Constipation | 4 (6) | 2 (4) | 6 (5)
Diarrhea | 4 (6) | 0 (0) | 4 (3)
Dyspepsia | 7 (10) | 3 (6) | 10 (8)
Flatulence | 21 (29) | 14 (29) | 35 (29)
Nausea | 13 (18) | 9 (19) | 22 (18)
Vomiting | 5 (7) | 1 (2) | 6 (5)
Metabolic and Nutritional
Peripheral Edema | 7 (10) | 6 (13) | 13 (11)
Musculoskeletal System
Arthralgia | 18 (25) | 13 (27) | 31 (26)
Myalgia | 20 (28) | 15 (31) | 35 (29)
Nervous System
Depression | 20 (28) | 18 (38) | 38 (32)
Dizziness | 8 (11) | 5 (10) | 13 (11)
Hypertonia | 4 (6) | 0 (0) | 4 (3)
Insomnia | 30 (42) | 23 (48) | 53 (44)
Leg Cramps | 7 (10) | 3 (6) | 10 (8)
Nervousness | 20 (28) | 20 (42) | 40 (33)
Paresthesia | 24 (33) | 15 (31) | 39 (33)
Vertigo | 12 (17) | 12 (25) | 24 (20)
Respiratory System
Cough Increased | 4 (6) | 1 (2) | 5 (4)
Pharyngitis | 6 (8) | 4 (8) | 10 (8)
Rhinitis | 6 (8) | 7 (15) | 13 (11)
Skin and Appendages
Rash | 3 (4) | 3 (6) | 6 (5)
Urogenital System
Breast Pain | 21 (29) | 7 (15) | 28 (23)
Dysmenorrhea | 4 (6) | 3 (6) | 7 (6)
Metorrhagia | 10 (14) | 3 (6) | 13 (11)

In a second 12-week clinical trial that included 52 women treated with 0.45 mg Cenestin and 51 women treated with placebo, adverse events that occurred at a rate of >5% are summarized in Table 6.

Table 6 Number (%) of Patients with a ≥ 5% Occurrence Rate By Body System and Treatment Group
Body System and Term | Cenestin 0.45 mg | Control | p-value
Any Adverse Event (%) | 40 (75.5%) | 39 (76.5%) | 1.0000
Body As A Whole | 20 (37.7%) | 24 (47.1%) | 0.4275
Asthenia | 6 (11.3%) | 7 (13.7%) | 0.7731
Headache | 6 (11.3%) | 8 (15.7%) | 0.5748
Infection | 1 (1.9%) | 6 (11.8%) | 0.0576
Pain | 6 (11.3%) | 1 (2.0%) | 0.1128
Pain abdominal | 5 (9.4%) | 3 (5.9%) | 0.7159
Cardiovascular | 5 (9.4%) | 10 (19.6%) | 0.1695
Palpitations | 3 (5.7%) | 3 (5.9%) | 1.0000
Vasodilations | 2 (3.8%) | 4 (7.8%) | 0.4324
Digestive | 8 (15.1%) | 7 (13.7%) | 1.0000
Nausea | 5 (9.4%) | 2 (3.9%) | 0.4374
Metabolic and Nutritional | 5 (9.4%) | 3 (5.9%) | 0.1759
Weight increase | 3 (5.7%) | 2 (3.9%) | 1.0000
Musculoskeletal | 5 (9.4%) | 6 (11.8%) | 0.7582
Arthralgia | 5 (9.4%) | 5 (9.8%) | 1.0000
Myalgia | 2 (3.8%) | 6 (11.8%) | 0.1566
Neurological | 15 (28.3%) | 19 (37.3%) | 0.4044
Anxiety | 3 (5.7%) | 1 (2.0%) | 0.6179
Depression | 2 (3.8%) | 7 (13.7%) | 0.0895
Insomnia | 3 (5.7%) | 5 (9.8%) | 0.4839
Nervousness | 2 (3.8%) | 7 (13.7%) | 0.0895
Paresthesia | 4 (7.5%) | 3 (5.9%) | 1.0000
Vertigo | 3 (5.7%) | 3 (5.9%) | 1.0000
Respiratory | 10 (18.9%) | 6 (11.8%) | 0.4173
Upper Respiratory Tract Infection | 7 (13.2%) | 1 (2.0%) | 0.0603
Rhinitis | 3 (5.7%) | 2 (3.9%) | 1.0000
Pharyngitis | 1 (1.9%) | 3 (5.9%) | 0.3581
Urogenital | 19 (35.8%) | 7 (13.7%) | 0.0124
Endometrial thickening | 10 (18.9%) | 4 (7.8%) | 0.1503
Vaginitis | 4 (7.5%) | 1 (2.0%) | 0.3632

P-value by Fisher's Exact (2-tail) Test

If a subject experiences the same event more than once, the first occurrence is tabulated.

The following additional adverse reactions have been reported with estrogen and/or progestin therapy:

1. Genitourinary system.
  Changes in vaginal bleeding pattern and abnormal withdrawal bleeding or flow; breakthrough bleeding; spotting; dysmenorrhea, increase in size of uterine leiomyomata; vaginitis, including vaginal candidiasis; change in amount of cervical secretion; changes in cervical ectropion; ovarian cancer; endometrial hyperplasia; endometrial cancer.
2. Breasts.
  Tenderness, enlargement, pain, nipple discharge, galactorrhea; fibrocystic breast changes; breast cancer.
3. Cardiovascular.
  Deep and superficial venous thrombosis; pulmonary embolism; thrombophlebitis; myocardial infarction; stroke; increase in blood pressure.
4. Gastrointestinal.
  Nausea, vomiting; abdominal cramps, bloating; cholestatic jaundice; increased incidence of gallbladder disease; pancreatitis, enlargement of hepatic hemangiomas.
5. Skin.
  Chloasma or melasma, which may persist when drug is discontinued; erythema multiforme; erythema nodosum; hemorrhagic eruption; loss of scalp hair; hirsutism; pruritus, rash.
6. Eyes.
  Retinal vascular thrombosis; intolerance to contact lenses.
7. Central nervous system.
  Headache; migraine; dizziness; mental depression; chorea; nervousness; mood disturbances; irritability; exacerbation of epilepsy, dementia.
8. Miscellaneous.
  Increase or decrease in weight; reduced carbohydrate tolerance; aggravation of porphyria; edema; arthalgias; leg cramps; changes in libido; urticaria, angioedema; anaphylactoid/anaphylactic reactions; hypocalcemia; exacerbation of asthma; increased triglycerides.

OVERDOSAGE

Serious ill effects have not been reported following acute ingestion of large doses of estrogen containing drug products by young children. Overdosage of estrogen may cause nausea and vomiting, and withdrawal bleeding may occur in females.

DOSAGE AND ADMINISTRATION

When estrogen is prescribed for a postmenopausal woman with a uterus, progestin should also be initiated to reduce the risk of endometrial cancer. A woman without a uterus does not need progestin. Use of estrogen, alone or in combination with a progestin, should be with the lowest effective dose and for the shortest duration consistent with treatment goals and risks for the individual woman. Patients should be reevaluated periodically as clinically appropriate (e.g., 3-month to 6-month intervals) to determine if treatment is still necessary (see BOXED WARNINGS and WARNINGS). For women who have a uterus, adequate diagnostic measures, such as endometrial sampling, when indicated, should be undertaken to rule out malignancy in cases of undiagnosed persistent or recurring abnormal vaginal bleeding.

1. For treatment of moderate to severe vasomotor symptoms associated with the menopause.

- Cenestin 0.45 mg
- Cenestin 0.625 mg
- Cenestin 0.9 mg
- Cenestin 1.25 mg
  Patients should be started at Cenestin 0.45 mg daily. Subsequent dosage adjustment may be made based upon the individual patient response. This dose should be periodically reassessed by the healthcare provider. The lowest effective dose of Cenestin for the treatment of moderate to severe vasomotor symptoms has not been determined.

2. For treatment of moderate to severe symptoms of vulvar and vaginal atrophy associated with the menopause. When prescribing solely for the treatment of symptoms of vulvar and vaginal atrophy, topical vaginal products should be considered.

- Cenestin 0.3 mg daily

HOW SUPPLIED

Cenestin (synthetic conjugated estrogens, A) Tablets are available as:

0.45 mg: | Round, orange, film-coated, and are debossed with letters, dp, and number, 46.; Available in bottles of:
 | 10 | NDC 54868-5415-1
 | 30 | NDC 54868-5415-0
0.625 mg: | Round, red, film-coated, and are debossed with letters, dp, and number, 42.; Available in bottles of:
 | 10 | NDC 54868-4879-1
 | 30 | NDC 54868-4879-2
 | 100 | NDC 54868-4879-0
1.25 mg: | Round, blue, film-coated, and are debossed with letters, dp, and number, 44.; Available in bottles of:
 | 10 | NDC 54868-1432-0
 | 30 | NDC 54868-1432-1

Store at 20-25°C (68-77°F); excursions are permitted to 15-30°C (59-86°F) [See USP Controlled Room Temperature].

Dispense in tight container.

Dispense in child-resistant packaging.

Keep out of the reach of children.

Pharmacist: Include one “Information for the patient” leaflet with each package dispensed.

PATIENT INFORMATION

Cenestin®

(synthetic conjugated estrogens, A) Tablets

Read this PATIENT INFORMATION before you start taking Cenestin and read what you get each time you refill Cenestin. There may be new information. This information does not take the place of talking to your healthcare provider about your medical condition or your treatment.

BOXED WARNING

WHAT IS THE MOST IMPORTANT INFORMATION I SHOULD KNOW ABOUT CENESTIN (SYNTHETIC ESTROGEN MIXTURE)?

• Estrogens increase the chances of getting cancer of the uterus.

Report any unusual vaginal bleeding right away while you are taking estrogens. Vaginal bleeding after menopause may be a warning sign of cancer of the uterus (womb).Your healthcare provider should check any unusual vaginal bleeding to find out the cause.

• Do not use estrogens with or without progestins to prevent heart disease, heart attacks, or strokes.

Using estrogens with or without progestins may increase your chances of getting heart attacks, strokes, breast cancer, and blood clots. Using estrogens with progestins may increase your risk of dementia. You and your healthcare provider should talk regularly about whether you still need treatment with Cenestin.

What is Cenestin?

Cenestin is a medicine that contains a mixture of synthetic estrogens made from a plant source.

What is Cenestin used for?

Cenestin is used after menopause to:

- reduce moderate or severe hot flashes.
  Estrogens are hormones made by a woman’s ovaries. The ovaries normally stop making estrogens when a woman is between 45 to 55 years old. This drop in body estrogen levels causes the “change of life” or menopause (the end of monthly menstrual periods). Sometimes, both ovaries are removed during an operation before natural menopause takes place. The sudden drop in estrogen levels causes “surgical menopause.”
  When estrogen levels begin dropping, some women develop very uncomfortable symptoms, such as feelings of warmth in the face, neck, and chest, or sudden strong feelings of heat and sweating (“hot flashes” or “hot flushes”). In some women, the symptoms are mild, and they will not need estrogens. In other women, symptoms can be more severe. You and your healthcare provider should talk regularly about whether you still need treatment with Cenestin.
- treat moderate to severe dryness, itching, and burning in and around the vagina. You and your healthcare provider should talk regularly about whether you still need treatment with Cenestin to control these problems. If you use Cenestin only to treat your dryness, itching, and burning in and around your vagina, talk with your healthcare provider about whether a topical vaginal product would be better for you.

Who Should Not Take Cenestin?

Do not start taking Cenestin if you:

- have unusual vaginal bleeding.
- currently have or have had certain cancers.
  Estrogens may increase the risk of certain types of cancers, including cancer of the breast or uterus. If you have or had cancer, talk with your healthcare provider about whether you should take Cenestin.
- had a stroke or heart attack in the past year.
- currently have or have had blood clots.
- currently have or have had liver problems.
- are allergic to Cenestin or any of its ingredients.
  See the end of this leaflet for a list of ingredients in Cenestin.
- if you think you may be pregnant.

Tell your healthcare provider:

- if you are breastfeeding.
  The synthetic estrogen hormones in Cenestin can pass into your milk.
- about all of your medical problems.
  Your healthcare provider may need to check you more carefully if you have certain conditions, such as asthma (wheezing), epilepsy (seizures), migraine, endometriosis, lupus, or problems with your heart, liver, thyroid, kidneys, or have high calcium levels in your blood.
- about all the medicines you take.
  This includes prescription and nonprescription medicines, vitamins, and herbal supplements. Some medicines may affect how Cenestin works. Cenestin may also affect how your other medicines work.
- if you are going to have surgery or will be on bedrest.
  You may need to stop taking estrogens.

How Should I Take Cenestin?

Take one Cenestin tablet each day at about the same time. If you miss a dose, take it as soon as possible. If it is almost time for your next dose, skip the missed dose and go back to your normal schedule. Do not take 2 doses at the same time.

Start at the lowest dose and talk to your healthcare provider about how well that dose is working for you. Estrogens should be used only as long as needed. You and your healthcare provider should talk regularly (for example every 3 to 6 months) about whether you still need treatment with Cenestin.

What are the possible side effects of estrogens?

Less common but serious side effects include:

- Breast cancer
- Blood clots
- Cancer of the uterus
- Dementia
- Gallbladder disease
- Stroke
- Ovarian cancer
- Heart attack

These are some of the warning signs of serious side effects:

- Breast lumps
- Chest pain
- Unusual vaginal bleeding
- Shortness of breath
- Dizziness and faintness
- Pains in your legs
- Changes in speech
- Changes in vision
- Severe headaches
- Vomiting

Call your healthcare provider right away if you get any of these warning signs, or any other unusual symptom that concerns you.

Common side effects include:

- Headache
- Stomach/abdominal cramps, bloating
- Breast pain
- Nausea and vomiting
- Irregular vaginal bleeding or spotting
- Hair loss

Other side effects include:

- High blood pressure
- Fluid retention
- Liver problems
- Enlargement of benign tumors of the uterus (“fibroids”)
- High blood sugar
- Vaginal yeast infection

These are not all the possible side effects of Cenestin. For more information, ask your healthcare provider or pharmacist.

What can I do to lower my chances of a serious side effect with Cenestin?

- Talk with your healthcare provider regularly about whether you should continue taking Cenestin.
- If you have a uterus, talk to your healthcare provider about whether the addition of a progestin is right for you.
- See your healthcare provider right away if you get vaginal bleeding while taking Cenestin.
- Have a breast exam and mammogram (breast X-ray) every year unless your healthcare provider tells you something else. If members of your family have had breast cancer or if you have ever had breast lumps or an abnormal mammogram, you may need to have breast exams more often.
- If you have high blood pressure, high cholesterol (fat in the blood), diabetes, are overweight, or if you use tobacco, you may have higher chances for getting heart disease. Ask your healthcare provider for ways to lower your chances for getting heart disease.

General information about safe and effective use of Cenestin.

Medicines are sometimes prescribed for conditions that are not mentioned in patient information leaflets. Do not take Cenestin for conditions for which it was not prescribed. Do not give Cenestin to other people, even if they have the same symptoms you have. It may harm them.

Keep Cenestin out of the reach of children.

This leaflet provides a summary of the most important information about Cenestin. If you would like more information, talk with your healthcare provider or pharmacist. You can ask for information about Cenestin that is written for health professionals. You can get more information by calling the toll free number 877-405-0369.

What are the ingredients in Cenestin?

Tablets for oral administration, are available in 0.3 mg, 0.45 mg, 0.625 mg, 0.9 mg and 1.25 mg strengths of synthetic conjugated estrogens, A. Tablets also contain the following inactive ingredients: ethylcellulose, hypromellose, lactose monohydrate, magnesium stearate, polyethylene glycol, polysorbate 80, pregelatinized starch, titanium dioxide, and triethyl citrate.

-0.3 mg tablets also contain FD&C Blue No. 2 aluminum lake and D&C Yellow No. 10 aluminum lake.

-0.45 mg tablets also contain FD&C Yellow No. 6/Sunset Yellow FCF lake.

-0.625 mg tablets also contain FD&C Red No. 40 aluminum lake.

-0.9 mg tablets do not contain any additional color additives.

-1.25 mg tablets also contain FD&C Blue No. 2 aluminum lake.

Manufactured By:

Duramed Pharmaceuticals, Inc.

Subsidiary of Barr Pharmaceuticals, Inc.

Pomona, New York 10970

Revised SEPTEMBER 2004

BR - 41, 46, 42, 43, 44

Relabeling and Repackaging by:
Physicians Total Care, Inc.
Tulsa, OK 74146

PACKAGE/LABEL PRINCIPAL DISPLAY PANEL - 0.45 mg

Cenestin®

(synthetic conjugated estrogens, A) Tablets

0.45 mg

Rx only

Each tablet contains:
Synthetic conjugated estrogens, A..........0.45 mg

Usual Dosage: See accompanying prescribing information.

Dispense in tight container.

Store at 20-25°C (68-77°F); excursions are permitted to 15-30°C (59-86°F) [See USP Controlled Room Temperature].

Pharmacist: Include one "Information for the patient" leaflet with each package dispensed. Dispense in child-resistant packaging.

Keep out of the reach of children.

PACKAGE/LABEL PRINCIPAL DISPLAY PANEL - 0.625 mg

Cenestin®

(synthetic conjugated estrogens, A) Tablets

0.625 mg

Each tablet contains:
Synthetic conjugated estrogens, A..........0.625 mg

Usual Dosage: See accompanying prescribing information.

Dispense in tight container.

Store at 20-25°C (68-77°F); excursions are permitted to 15-30°C (59-86°F) [See USP Controlled Room Temperature].

Pharmacist: Include one "Information for the patient" leaflet with each package dispensed. Dispense in child-resistant packaging.

Keep out of the reach of children.

PACKAGE/LABEL PRINCIPAL DISPLAY PANEL - 1.25 mg

Cenestin®

(synthetic conjugated estrogens, A) Tablets

1.25 mg

Rx only

Each tablet contains:
Synthetic conjugated estrogens, A..........1.25 mg

Usual Dosage: See accompanying prescribing information.

Dispense in tight container.

Store at 20-25°C (68-77°F); excursions are permitted to 15-30°C (59-86°F) [See USP Controlled Room Temperature].

Pharmacist: Include one "Information for the patient" leaflet with each package dispensed. Dispense in child-resistant packaging.

Keep out of the reach of children.